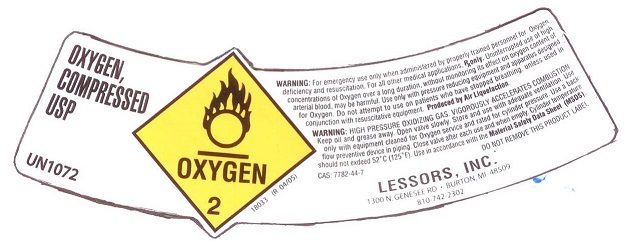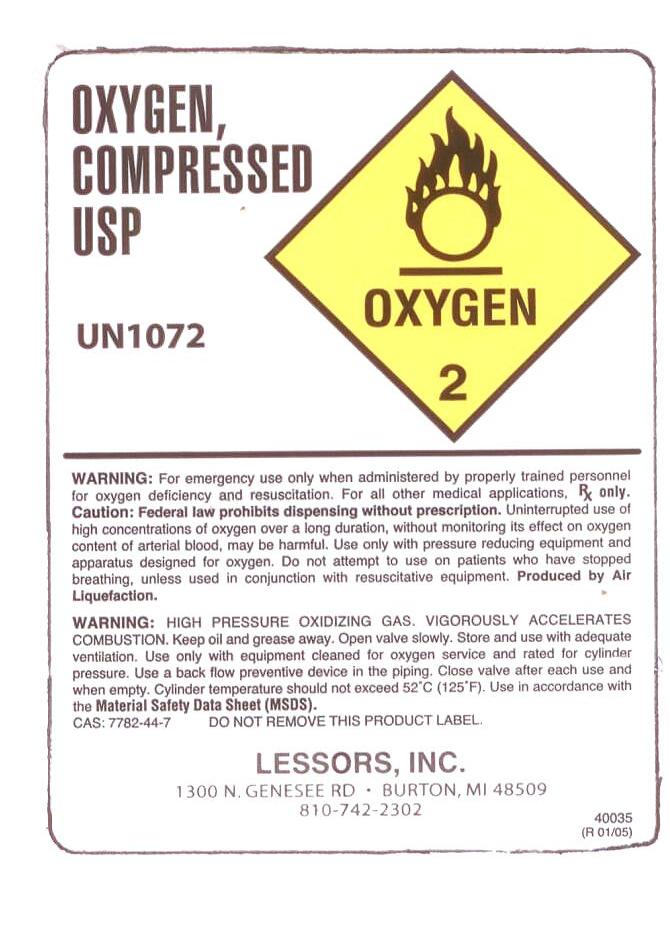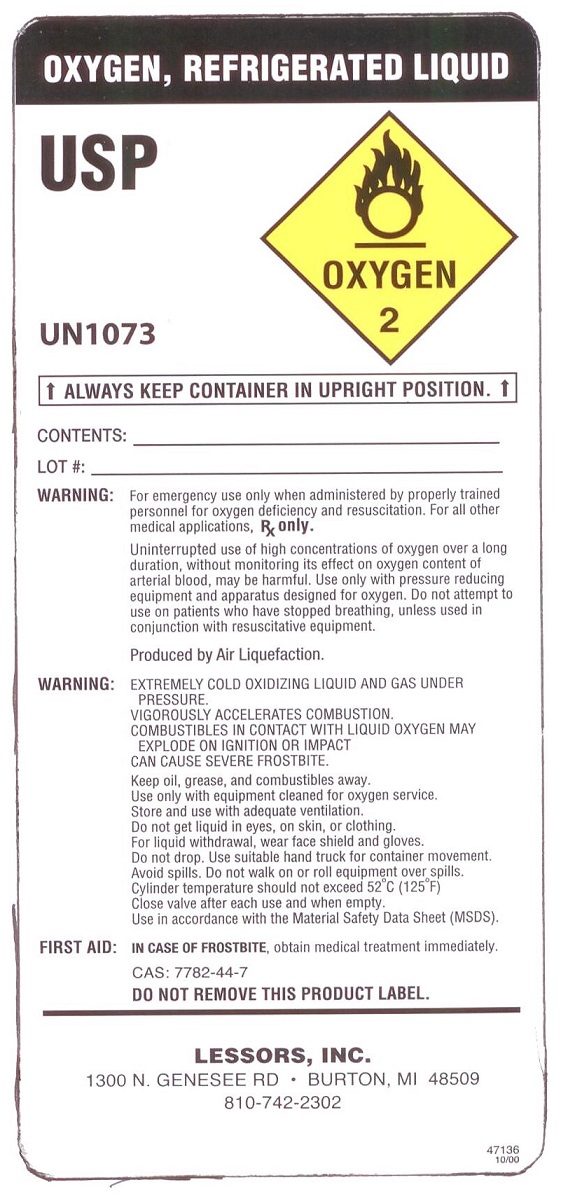 DRUG LABEL: Oxygen
NDC: 55404-001 | Form: GAS
Manufacturer: Lessors, Incorporated
Category: prescription | Type: HUMAN PRESCRIPTION DRUG LABEL
Date: 20241107

ACTIVE INGREDIENTS: OXYGEN 995 mL/1 L

oxygen

PACKAGE LABEL

OXYGEN, COMPRESSED USP UN1072
OXYGEN 2
WARNING: For emergency use only when administered by properly trained personnel for oxygen deficiency and resuscitation. For all other medical applications, Rx only.
CAUTION: Federal law prohibits dispensing without prescription. Uninterrupted use of high concentrations of oxygen over a long duration, without monitoring its effect on oxygen content of arterial blood, may be harmful. Use only with pressure reducing equipment and apparatus designed for oxygen. Do not attempt to use on patients who have stopped breathing, unless used in conjunction with resuscitative equipment. Produced by Air Liquefaction.
WARNING: HIGH PRESSURE OXIDIZING GAS. VIGOROUSLY ACCELERATES COMBUSTION. Keep oil, grease away. Open valve slowly. Store and use with adequate ventilation. Use only with equipment cleaned for oxygen service and rated for cylinder pressure. Use back flow preventive device in the piping. Close valve after each use and when empty. Cylinder temperature should not exceed 52C (125F). Use in accordance with the Material Safety Data Sheets (MSDS). CAS: 7782-44-7 DO NOT REMOVE THIS PRODUCT LABEL.
LESSORS, INC. 1300 N. GENESEE RD. BURTON, MI 48509 810-742-2302
40035 (R 01/05)

PACKAGE LABEL

OXYGEN, REFRIGERATED USP UN1073
OXYGEN 2
ALWAYS KEEP CONTAINER IN UPRIGHT POSITION
CONTENTS:
LOT #:
WARNING: For emergency use only when administered by properly trained personnel for oxygen deficiency and resuscitation. For all other medical applications, Rx only.
Uninterrupted use of high concentrations of oxygen over a long duration, without monitoring its effect on oxygen content of arterial blood, may be harmful. Use only with pressure reducing equipment and apparatus designed for oxygen. Do not attempt to use on patients who have stopped breathing, unless used in conjunction with resuscitative equipment. Produced by Air Liquefaction.
WARNING: EXTREMELY COLD OXIDIZING LIQUID AND GAS UNDER PRESSURE. VIGOROUSLY ACCELERATES COMBUSTION. Keep oil, grease, and combustibles away. Use only with equipment cleaned for oxygen service. Store and use with adequate ventilation. Do not get liquid in eyes, on skin, or clothing. For liquid withdrawal, wear face shield and gloves. Do not drop. Use suitable hand truck for container movement. Avoid spills. Do not walk on or roll equipment over spills. Cylinder temperature should not exceed 52C (125F).Close valve after each use and when empty. Use in accordance with the Material Safety Data Sheets (MSDS).
FIRST AID: IN CASE OF FROSTBITE, obtain medical treatment immediately. CAS: 7782-44-7 DO NOT REMOVE THIS PRODUCT LABEL.
LESSORS, INC. 1300 N. GENESEE RD. BURTON, MI 48509 810-742-2302
47136 10/00

PACKAGE LABEL

OXYGEN, COMPRESSED USP UN1072
OXYGEN 2 18033 (R 04/05)
WARNING: For emergency use only when administered by properly trained personnel for oxygen deficiency and resuscitation.
For all other medical applications, Rx only.
CAUTION: Federal law prohibits dispensing without prescription. Uninterrupted use of high concentrations of oxygen over a long duration, without monitoring its effect on oxygen content of arterial blood, may be harmful. Use only with pressure reducing equipment and apparatus designed for oxygen. Do not attempt to use on patients who have stopped breathing, unless used in conjunction with resuscitative equipment. Produced by Air Liquefaction.
WARNING: HIGH PRESSURE OXIDIZING GAS. VIGOROUSLY ACCELERATES COMBUSTION. Keep oil and grease away. Open valve slowly. Store and use with adequate ventilation. Use only with equipment cleaned for oxygen service and rated for cylinder pressure. Use a back flow preventive device in the piping. Close valve after each use and when empty. Cylinder temperature should not exceed 52C (125F). Use in accordance with the Material Safety Data Sheets (MSDS). CAS: 7782-44-7 DO NOT REMOVE THIS PRODUCT LABEL.
LESSORS, INC. 1300 N. GENESEE RD. BURTON, MI 48509 810-742-2302